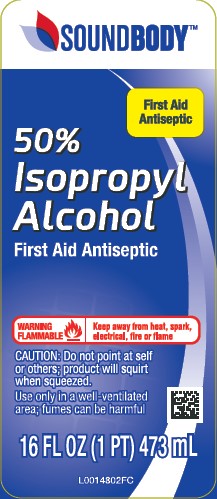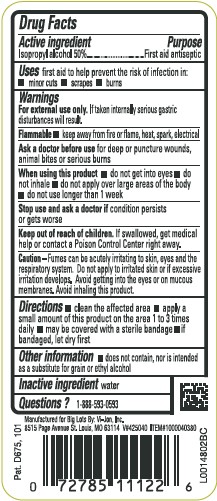 DRUG LABEL: 50% Rubbing
NDC: 50594-864 | Form: LIQUID
Manufacturer: Big Lots Stores, Inc.
Category: otc | Type: HUMAN OTC DRUG LABEL
Date: 20260129

ACTIVE INGREDIENTS: ISOPROPYL ALCOHOL 50 mL/100 mL
INACTIVE INGREDIENTS: WATER

Sound Body 864.003/864AC
Isopropyl Alcohol 50%

Active ingredient

Isopropyl alcohol 50%

Purpose

First aid antiseptic

Use

first aid to help prevent the risk of infection in:

- minor cuts
- scrapes
- burns

Warnings

For external use only.If taken internally serious gastic disturbances will result.

Flammable

- keep away from fire or flame, heat spark, electrical

Ask a doctor before use

for deep or puncture wounds, animal bites or serious burns

When using this product

- do not get into eyes
- do not inhale
- do not apply over large areas of the body
- do not use longer than 1 week

Stop use and ask a doctor

if condition persists or gets worse

keep out of reach of children

If swallowed, get medical help or contact a Poison Control Center right away.

Caution

Fumes can be acutely irritating to skin, eyes and the respiratory system. Do not apply to irritated skin or if excessive irritation develops. Avoid getting into eyes or on mucous membranes. Avoid inhaling this product.

Directions

- clean the affected area
- apply a small amount of the is product on the affected area 1 to 3 times daily
- may be covered with a sterile bandage
- if bandaged, let dry first

Other Information

- does not contain, nor is intended as a substitute for grain or ethyl alcohol

Inactive ingredient

water

Questions?

1-888-593-0593

ADVERSE REACTION

Manufactured for Big Lots By: Vi-Jon, Inc.

8515 Page Avenue St. Louis, MO 63114

Pat. D675, 101

principal display panel

SOUND BODY™

FIRST AID ANTISPETIC

50%

Isopropyl

Alcohol

First Aid Antispetic

WARNING FLAMMABLE - Keep away from heat, spark, electrical, fire or flame

CAUTION: Do not point at self or others; product will squirt when squeezed.

Use only in a well-ventilated area; fumes can be harmful

16 FL OZ (1 PT) 473 mL